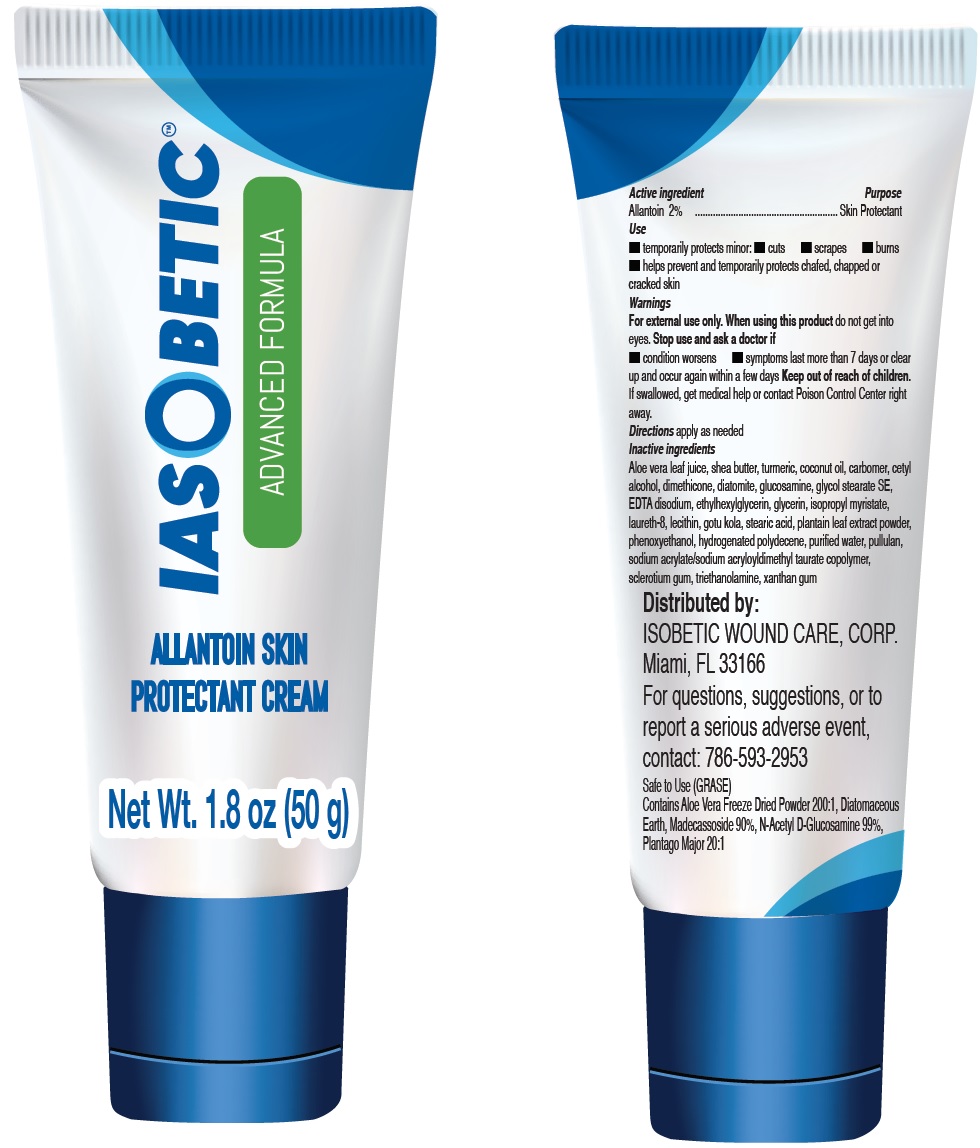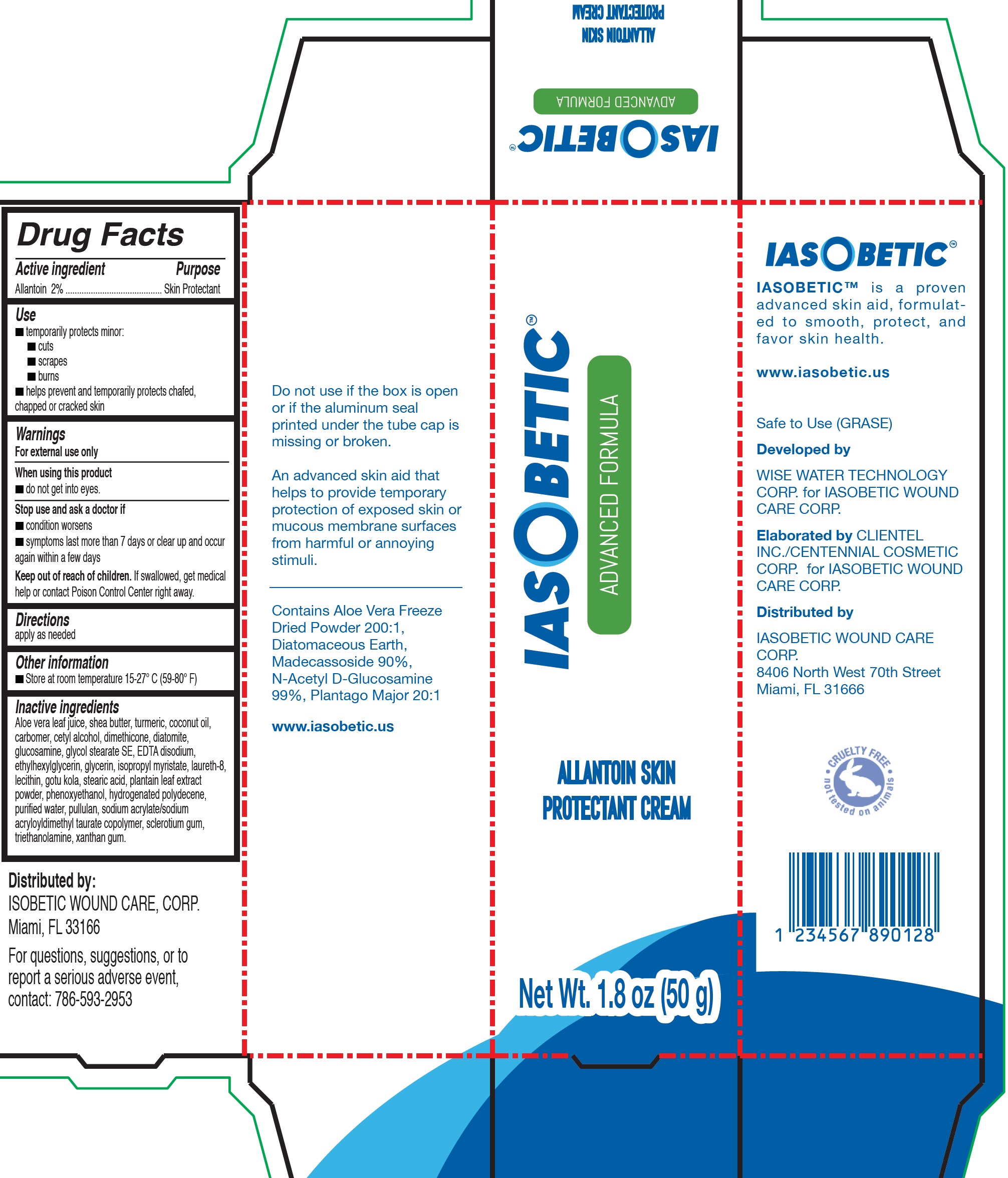 DRUG LABEL: IASOBETIC Allantoin Skin Protectant
NDC: 72904-001 | Form: CREAM
Manufacturer: IASOBETIC WOUND CARE CORP.
Category: otc | Type: HUMAN OTC DRUG LABEL
Date: 20200214

ACTIVE INGREDIENTS: ALLANTOIN 20 mg/1 g
INACTIVE INGREDIENTS: ALOE VERA LEAF; SHEA BUTTER; TURMERIC; COCONUT OIL; CARBOMER HOMOPOLYMER, UNSPECIFIED TYPE; CETYL ALCOHOL; DIMETHICONE; DIATOMACEOUS EARTH; GLUCOSAMINE; GLYCOL STEARATE SE; EDETATE DISODIUM; ETHYLHEXYLGLYCERIN; GLYCERIN; ISOPROPYL MYRISTATE; LAURETH-8; CENTELLA ASIATICA LEAF; STEARIC ACID; PHENOXYETHANOL; WATER; PULLULAN; SODIUM ACRYLATE/SODIUM ACRYLOYLDIMETHYLTAURATE COPOLYMER (4000000 MW); BETASIZOFIRAN; TROLAMINE; XANTHAN GUM

IASOBETIC Allantoin Skin Protectant Cream

Active ingredient

Allantoin 2%

Purpose

Skin Protectant

Use

- temporarily protects minor:
- cuts
- scrapes
- burns
- helps prevent and temporarily protects chafed, chapped or cracked skin

Warnings

For external use only

When using this product

- do not get into eyes.

Stop use and ask a doctor if

- condition worsens
- symptoms last more than 7 days or clear up and occur again within a few days

Keep out of reach of children.

If swallowed, get medical help or contact Poison Control Center right away.

Directions

apply as needed

Other information

Store at room temperature 15-27° C (59-80° F)

Inactive ingredients

Aloe vera leaf juice, shea butter, turmeric, coconut oil, carbomer, cetyl alcohol, dimethicone, diatomite, glucosamine, glycol stearate SE, EDTA disodium, ethylhexylglycerin, glycerin, isopropyl myristate, laureth-8, lecithin, gotu kola, stearic acid, plantain leaf extract powder, phenoxyethanol, hydrogenated polydecene, purified water, pullulan, sodium acrylate/sodium acryloyldimethyl taurate copolymer, sclerotium gum, triethanolamine, xanthan gum.